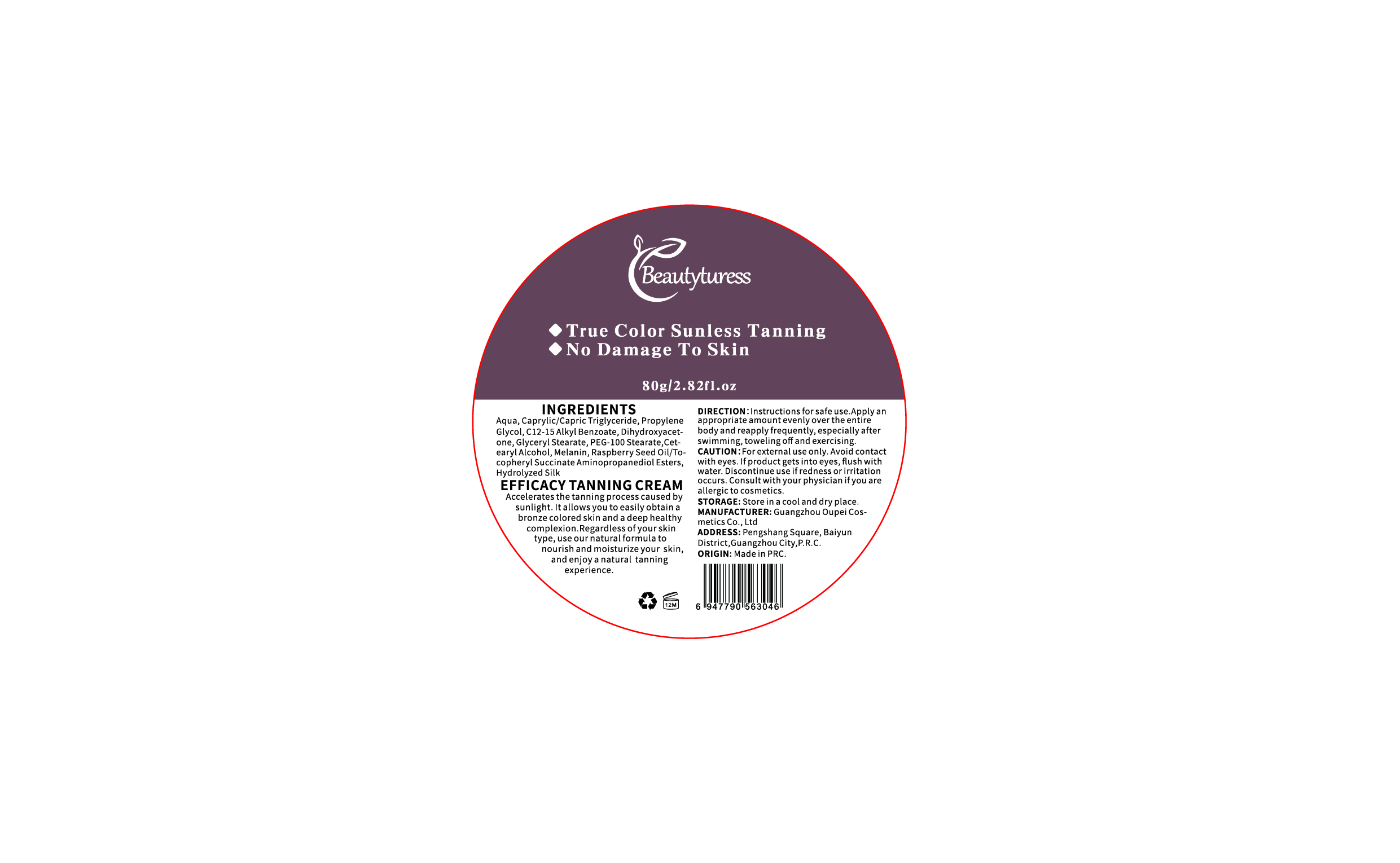 DRUG LABEL: Beautyturess 80g Shiny Tanning Cream
NDC: 84753-013 | Form: EMULSION
Manufacturer: Guangdong Bisutang Biotechnology Co., Ltd.
Category: otc | Type: HUMAN OTC DRUG LABEL
Date: 20241015

ACTIVE INGREDIENTS: DIGLYCERIN 4 g/80 g
INACTIVE INGREDIENTS: GLYCERYL STEARATE SE; DIHYDROXYACETONE; DIMETHICONE 100; DIAZOLIDINYL UREA; DIPROPYLENE GLYCOL; POLYACRYLAMIDE (10000 MW); 1,2-HEXANEDIOL; WATER; ALLANTOIN; ASCORBIC ACID

ACTIVE INGREDIENT

GLYCERIN

DIHYDROXYACETONE

PURPOSE

The primary purpose of a tanning cream is to accelerate and enhance the tanning process during sun exposure or tanning sessions. It helps achieve a more even, bronze or darker skin tone, while moisturizing and protecting the skin during the process. Some tanning creams may also provide mild sun protection or antioxidant properties to reduce the risk of sun damage.

Ask Doctor

If you have a history of skin allergies or have sensitive skin, it is advisable to consult a doctor before using this product.

DOSAGE AND ADMINISTRATION

Apply once daily to clean face and neck, avoiding the eye area

WHEN USING

Avoid contact with eyes and broken skin. If redness, swelling, or irritation occurs, discontinue use immediately and seek medical advice.

WARNINGS

Risk InformationFor external use only
Mention de risquesPour usage externe seulement
Do not use on damaged or broken skin.
Ne pas utiliser sur la peau endommagée ou avec des lésions
If rash occurs, discontinue use and consult a health care practitioner.
En présence d'une éruption cutanée, cesser l'utilisation et consulter un praticien de soins de santé
When using this product keep out of eyes. Rinse with water to remove.
Eviter tout contact avec les yeux. Rincer a l'eau le cas échéant
Keep out of reach of children. If swallowed, get medical help or contact a Poison Control Center right away.
Tenir hors de portée des enfants
En cas d'ingestion, consulter un médecin ou appeler un centre antipoison immédiatement.

INDICATIONS AND USAGE

Temporarily protects and helps relieve dry or cracked skin
Beneficlal for face, hands, body, and legs

Keep out of reach of children. If swallowed, get medical help or contact a Poison Control Center right away.
Tenir hors de portée des enfants
En cas d'ingestion, consulter un médecin ou appeler un centre antipoison immédiatement.

INACTIVE INGREDIENT

WATER

CAPRYLIC/CAPRIC TRIGLYCERIDE

PROPYLENE GLYCOL

CETEARYL ALCOHOL

GLYCERYL STEARATE

PEG-100 STEARATE

DIHYDROXYACETONE

C12-15 ALKYL BENZOATE

DIMETHICONE

POLYACRYLAMIDE

C13-14 ISOPARAFFIN

LAURETH-7

WATER

SYNTHETIC FLUORPHLOGOPITE

TITANIUM DIOXIDE

TIN OXIDE

1,2-HEXANEDIOL

POLYACRYLAMIDE

WATER

C13-14 ISOPARAFFIN

LAURETH-7

METHYLPARABEN

TOCOPHERYL ACETATE

BUTYLENE GLYCOL

WATER

CENTELLA ASIATICA EXTRACT

POLYGONUM CUSPIDATUM ROOT EXTRACT

SCUTELLARIA BAICALENSIS ROOT EXTRACT

CAMELLIA SINENSIS LEAF EXTRACT

GLYCYRRHIZA GLABRA (LICORICE) ROOT EXTRACT

CHAMOMILLA RECUTITA (MATRICARIA) FLOWER EXTRACT

ROSMARINUS OFFICINALIS (ROSEMARY) LEAF EXTRACT

FRAGRANCE

GLYCERETH-26